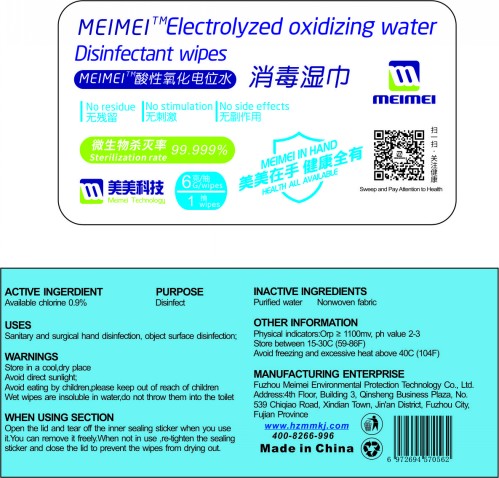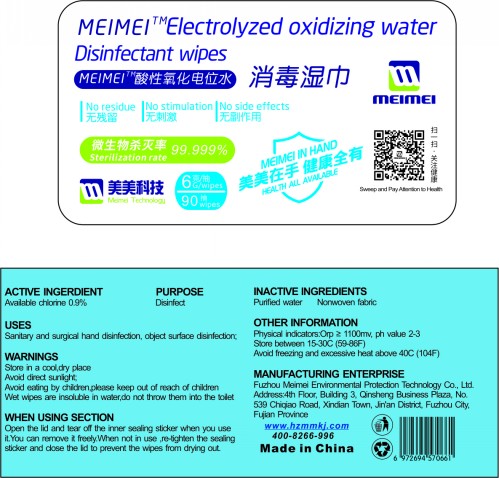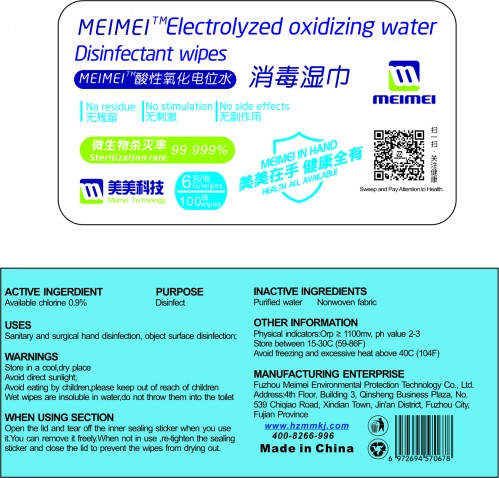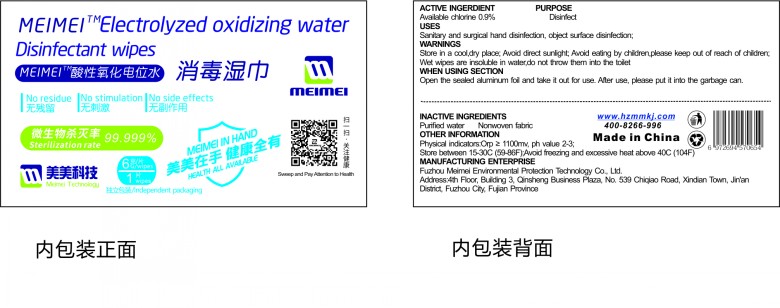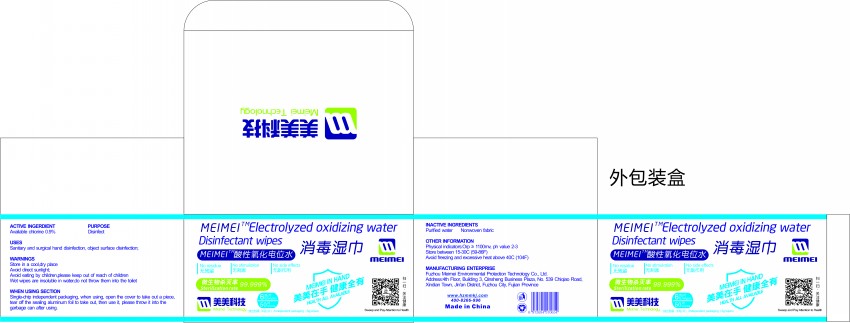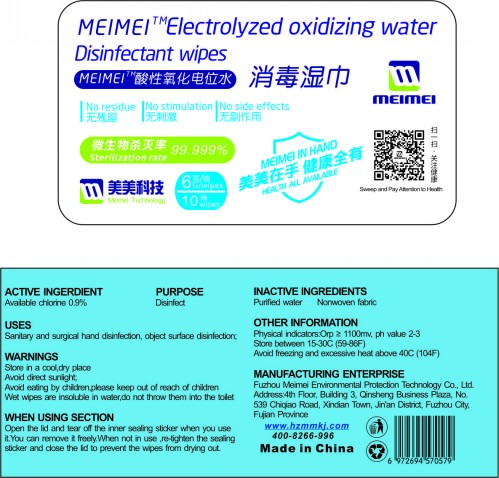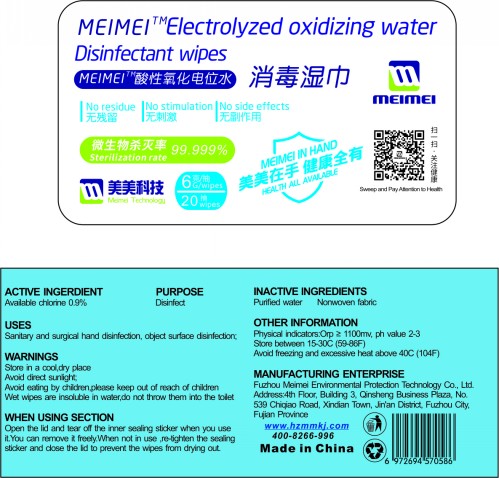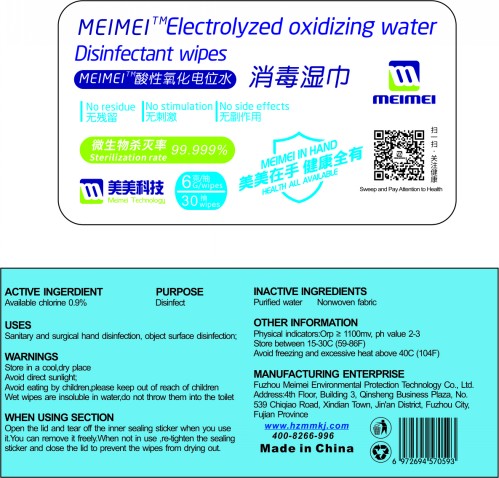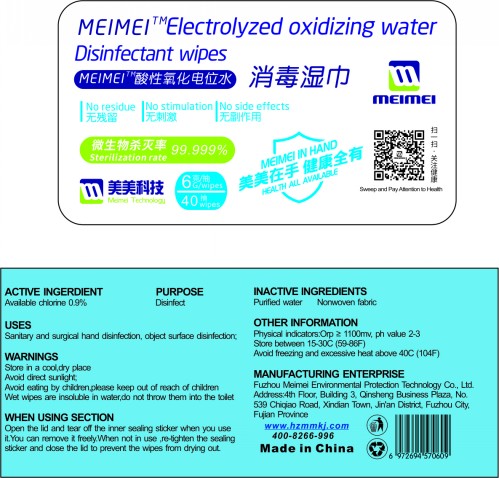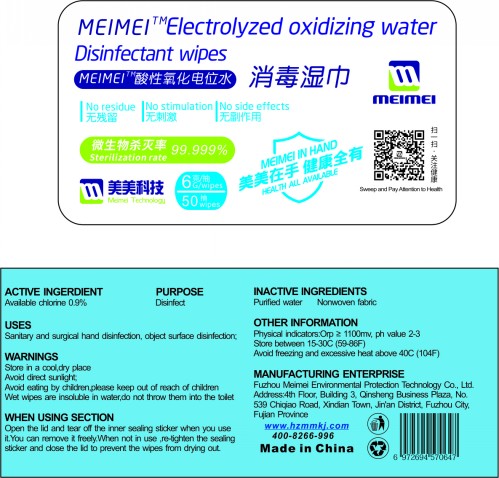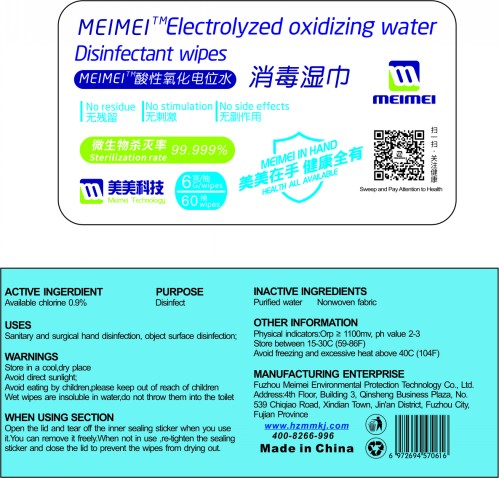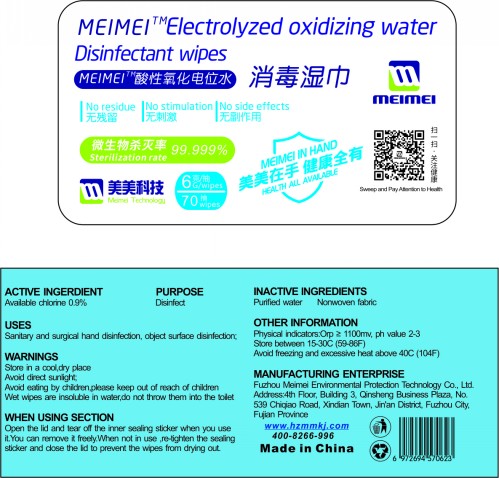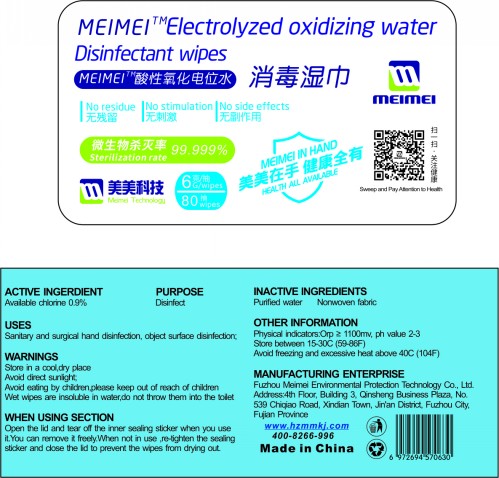 DRUG LABEL: Acid oxidation potential water disinfection wet towel
NDC: 75430-012 | Form: CLOTH
Manufacturer: Fuzhou Meimei Environmental Protection Technology Co.,Ltd.
Category: otc | Type: HUMAN OTC DRUG LABEL
Date: 20220328

ACTIVE INGREDIENTS: HYPOCHLOROUS ACID 0.9 g/100 g
INACTIVE INGREDIENTS: WATER

Acid oxidation potential water disinfection wet towel

ACTIVE INGERDIENT

Available chlorine 0.9%

PURPOSE

Disinfect

USES

Sanitary and surgical hand disinfection,object surface disinfection;

WARNINGS

Store in a cool ,dry place

Avoid direct sunlight;

Avoid eating by children, please keep out of reach of children

Wet wipes are insoluble in water ,do not throw them into the toilet

WHEN USING SECTION

Open the lid and tear off the inner sealing sticker when you use it.You can remove it freely.
When not in use , re-tighten the sealing sticker and close the lid to prevent the wipes from drying out.

OTHER INFORMATION

Physical indicators:Orp≥1100mv, ph value 2-3

Store between 15-30C(59-86F)

Avoid freezing and excessive heat above 40C(104F)

INACTIVE INGREDIENTS

Purified water, Nonwoven fabric